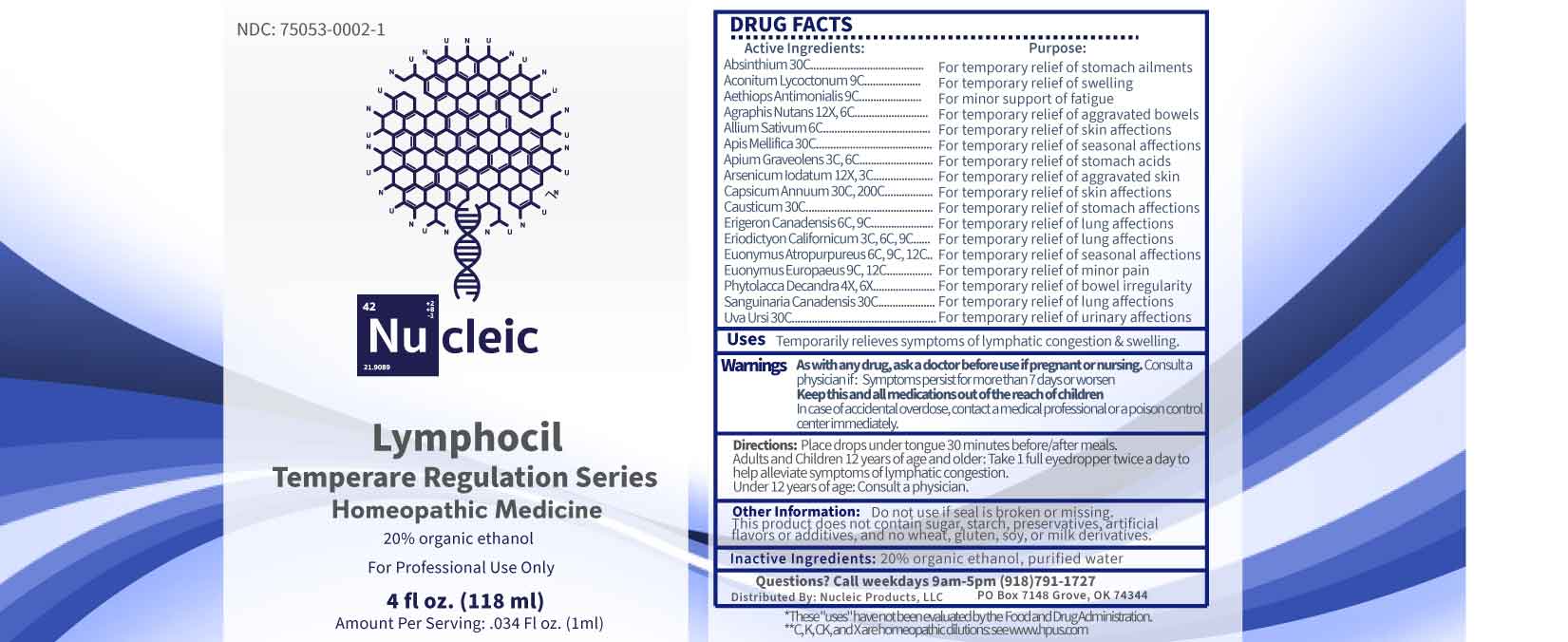 DRUG LABEL: Lymphocil
NDC: 75053-0002 | Form: LIQUID
Manufacturer: Nucleic Products, LLC
Category: homeopathic | Type: HUMAN OTC DRUG LABEL
Date: 20251124

ACTIVE INGREDIENTS: PHYTOLACCA AMERICANA ROOT 4 [hp_X]/1 mL; ARSENIC TRIIODIDE 12 [hp_X]/1 mL; HYACINTHOIDES NON-SCRIPTA WHOLE 12 [hp_X]/1 mL; CELERY SEED 3 [hp_C]/1 mL; ERIODICTYON CALIFORNICUM LEAF 3 [hp_C]/1 mL; GARLIC 6 [hp_C]/1 mL; ERIGERON CANADENSIS WHOLE 6 [hp_C]/1 mL; EUONYMUS ATROPURPUREUS BRANCH BARK/ROOT BARK 6 [hp_C]/1 mL; ACONITUM LYCOCTONUM WHOLE 9 [hp_C]/1 mL; MERCURIC SULFIDE 9 [hp_C]/1 mL; EUONYMUS EUROPAEUS SEED 9 [hp_C]/1 mL; WORMWOOD 30 [hp_C]/1 mL; APIS MELLIFERA 30 [hp_C]/1 mL; CAUSTICUM 30 [hp_C]/1 mL; SANGUINARIA CANADENSIS ROOT 30 [hp_C]/1 mL; ARCTOSTAPHYLOS UVA-URSI LEAF 30 [hp_C]/1 mL; CAPSICUM 30 [hp_C]/1 mL
INACTIVE INGREDIENTS: WATER; ALCOHOL

DRUG FACTS:

ACTIVE INGREDIENTS:

Absinthium 30C, Aconitum Lycoctonum 9C, Aethiops Antimonialis 9C, Agraphis Nutans 12X, 6C, Allium Sativum 6C, Apis Mellifica 30C, Apium Graveolens 3C, 6C, Arsenicum Iodatum 12X, 3C, Capsicum Annuum 30C, 200C, Causticum 30C, Erigeron Canadensis 6C, 9C, Eriodictyon Californicum 3C, 6C, 9C, Euonymus Atropurpureus 6C, 9C, 12C, Euonymus Europaeus 9C, 12C, Phytolacca Decandra 4X, 6X, Sanguinaria Canadensis 30C, Uva Ursi 30C.

PURPOSE:

Absinthium – For temporary relief of stomach ailments, Aconitum Lycoctonum - For temporary relief of swelling, Aethiops Antimonialis – For minor support of fatigue, Agraphis Nutans - For temporary relief of aggravated bowels, Allium Sativum - For temporary relief of skin affections, Apis Mellifica - For temporary relief of seasonal affections, Apium Graveolens - For temporary relief of stomach acids, Arsenicum Iodatum - For temporary relief of aggravated skin, Capsicum Annuum - For temporary relief of skin affections, Causticum - For temporary relief of stomach affections, Erigeron Canadensis - For temporary relief of lung affections, Eriodictyon Californicum - For temporary relief of lung affections, Euonymus Atropurpureus - For temporary relief of seasonal affections, Euonymus Europaeus - For temporary relief of minor pain, Phytolacca Decandra - For temporary relief of bowel irregularity, Sanguinaria Canadensis - For temporary relief of lung affections, Uva Ursi - For temporary relief of urinary affections

USES:

Temporarily relieves symptoms of lymphatic congestions and swelling.

Claims based on homeopathic theory, not accepted medical evidence. Not FDA evaluated.

*These "uses" have not been evaluated by the Food and Drug Administration.

**C, K, CK, and X are homeopathic dilutions see www.hpus.com

WARNINGS:

As with any drug, ask a doctor before use if pregnant or nursing.

Consult a physician if: Symptoms persist for more than 7 days or worsen.

Keep this and all medications out of reach of children.

In case of accidental overdose, contact a medical professional or poison control center immediately.

Do not use if seal is broken or missing.

This Product does not contain sugar, starch, preservatives, artificial flavors or additives, and no wheat, gluten, soy or milk derivatives.

KEEP OUT OF REACH OF CHILDREN:

In case of accidental overdose, contact a medical professional or poison control center immediately.

DIRECTIONS:

Place drops under tongue 30 minutes before/after meals.

Adults and children 12 years of age and older: Take 1 full eyedropper twice a day to help alleviate symptoms of lymphatic congestion.

Under 12 years of age: Consult a physician.

INACTIVE INGREDIENTS

20% organic ethanol, purified water

QUESTIONS:

Distributed By:

Nucleic Products, LLC

PO Box 7148 Grove, OK 74344

Call weekdays 9am-5pm (918)791-1727

PACKAGE LABEL DISPLAY:

NDC: 75053-0002-1

Nu cleic

Lymphocil

Temperare Regulation Series

Homeopathic Medicine

For Professional Use Only

4 fl oz. (118 ml)